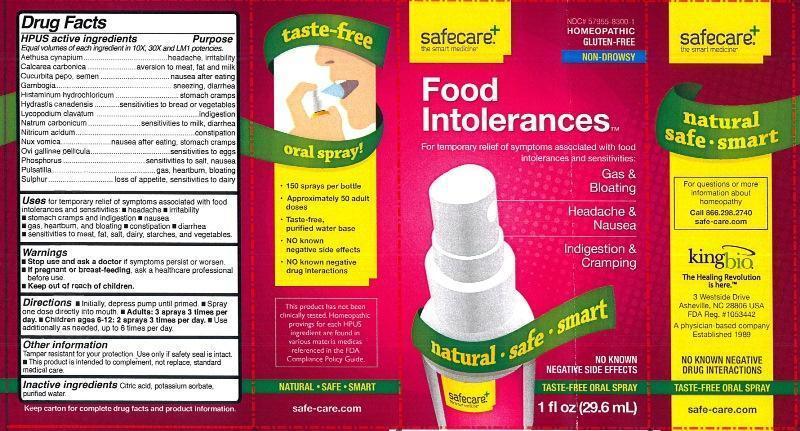 DRUG LABEL: Food Intolerances
NDC: 57955-8300 | Form: LIQUID
Manufacturer: King Bio Inc.
Category: homeopathic | Type: HUMAN OTC DRUG LABEL
Date: 20131104

ACTIVE INGREDIENTS: AETHUSA CYNAPIUM 10 [hp_X]/29.6 mL; OYSTER SHELL CALCIUM CARBONATE, CRUDE 10 [hp_X]/29.6 mL; PUMPKIN SEED 10 [hp_X]/29.6 mL; GAMBOGE 10 [hp_X]/29.6 mL; HISTAMINE DIHYDROCHLORIDE 10 [hp_X]/29.6 mL; GOLDENSEAL 10 [hp_X]/29.6 mL; LYCOPODIUM CLAVATUM SPORE 10 [hp_X]/29.6 mL; SODIUM CARBONATE 10 [hp_X]/29.6 mL; NITRIC ACID 10 [hp_X]/29.6 mL; STRYCHNOS NUX-VOMICA SEED 10 [hp_X]/29.6 mL; EGG SHELL MEMBRANE 10 [hp_X]/29.6 mL; PHOSPHORUS 10 [hp_X]/29.6 mL; PULSATILLA VULGARIS 10 [hp_X]/29.6 mL; SULFUR 10 [hp_X]/29.6 mL
INACTIVE INGREDIENTS: CITRIC ACID MONOHYDRATE; POTASSIUM SORBATE; WATER

Food Intolerances™

Drug Facts

____________________________________________________________________________________________________________

Equal volumes of each ingredient in 10X, 30X, and LM1 potencies.

HPUS active ingredients: Aethusa cynapium, Calcarea carbonica, Cucurbita pepo, semen, Gambogia, Histaminum hydrochloricum, Hydrastis canadensis, Lycopodium clavatum, Natrum carbonicum, Nitricum acidum, Nux vomica, Ovi gallinae pellicula, Phosphorus, Pulsatilla, Sulphur.

INDICATIONS AND USAGE

Uses for temporary relief of symptoms associated with food intolerances and sensitivities:

- headache
- irritability
- stomach cramps and indigestion
- nausea
- gas, heartburn and bloating
- constipation
- diarrhea
- sensitivities to meat, fat, salt, dairy, starches and vegetables.

Warnings

- Stop use and ask a doctor if symptoms persist or worsen.
- If pregnant or breast-feeding, ask a healthcare professional before use.

- Keep out of reach of children.

Directions:

- Initially, depress pump until primed.
- Spray one dose directly into mouth.
- Adults: 3 sprays 3 times per day.
- Children ages 6-12: 2 sprays 3 times per day.
- Use additionally as needed, up to 6 times per day.

OTHER SAFETY INFORMATION

Tamper resistant for your protection. Use only if safety seal is intact.

- This product is intended to complement, not replace, standard medical care.

Inactive Ingredients: Citric acid, potassium sorbate, purified water.

Drug Facts

__________________________________________________________________________________________________________________

HPUS active ingredients Purpose

Equal volumes of each ingredient in 10X, 30X, and LM1 potencies.

Aethusa cynapium..........................................................................headache, irritability

Calcarea carbonica.........................................................................aversion to meat, fat and milk

Cucurbita pepo, semen...................................................................nausea after eating

Gambogia.....................................................................................sneezing, diarrhea

Histaminum hydrochloricum............................................................stomach cramps

Hydrastis canadensis......................................................................sensitivities to bread or vegetables

Lycopodium clavatum.....................................................................indigestion

Natrum carbonicum........................................................................sensitivities to milk, diarrhea

Nitricum acidum.............................................................................constipation

Nux vomica...................................................................................nausea after eating, stomach cramps

Ovi gallinae pellicula.......................................................................sensitivities to eggs

Phosphorus....................................................................................sensitivities to salt, nausea

Pulsatilla........................................................................................gas, heartburn, bloating

Sulphur..........................................................................................loss of appetite, sensitivities to dairy